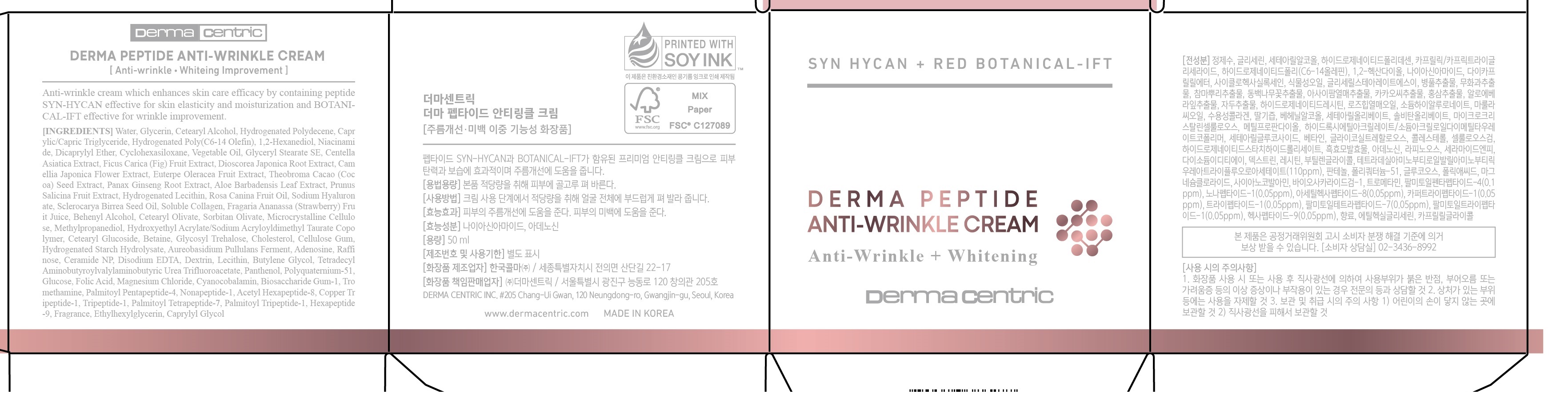 DRUG LABEL: DERMA PEPTIDE ANTI-WRINKLE
NDC: 79593-0007 | Form: CREAM
Manufacturer: DERMA CENTRIC INC
Category: otc | Type: HUMAN OTC DRUG LABEL
Date: 20210328

ACTIVE INGREDIENTS: ADENOSINE 0.044 g/100 mL; NIACINAMIDE 2 g/100 mL
INACTIVE INGREDIENTS: WATER; GLYCERIN

ACTIVE INGREDIENT

niacinamide, adenosine

PURPOSE

anti-wrinkle, whitening improvement

KEEP OUT OF REACH OF THE CHILDREN

WARNINGS

■ For external use only.

■ Do not use in eyes.

■ lf swallowed, get medical help promptly.

■ Stop use, ask doctor lf irritation occurs.

■ Keep out of reach of children.

DOSAGE AND ADMINISTRATION

for external use only

INACTIVE INGREDIENT

WATER
GLYCERIN
HYDROGENATED POLYDECENE
HYDROGENATED POLY(C6-14 OLEFIN)
CAPRYLIC/CAPRIC TRIGLYCERIDE
CETEARYL ALCOHOL
1,2-HEXANEDIOL
GLYCERIN
WATER
TETRADECYL AMINOBUTYROYLVALYLAMINOBUTYRIC UREA TRIFLUOROACETATE
MAGNESIUM CHLORIDE
WATER
METHYLPROPANEDIOL
DIOSCOREA JAPONICA ROOT EXTRACT
GLYCERIN
GLYCOSYL TREHALOSE
HYDROGENATED STARCH HYDROLYSATE
1,2-HEXANEDIOL
RAFFINOSE
LECITHIN
POLYQUATERNIUM-51
BIOSACCHARIDE GUM-1
BEHENYL ALCOHOL
CETEARYL ALCOHOL
HYDROGENATED LECITHIN
GLYCERYL STEARATE SE
CHOLESTEROL
CERAMIDE NP
NIACINAMIDE
VEGETABLE OIL
CYCLOHEXASILOXANE
DICAPRYLYL ETHER
CETEARYL ALCOHOL
CETEARYL GLUCOSIDE
GLUCOSE
WATER
CETEARYL OLIVATE
SORBITAN OLIVATE
GLYCERYL STEARATE SE
GLYCERIN
BUTYLENE GLYCOL
WATER
HYDROGENATED LECITHIN
CENTELLA ASIATICA EXTRACT
FICUS CARICA (FIG) FRUIT EXTRACT
1,2-HEXANEDIOL
CERAMIDE NP
FRAGRANCE
BETAINE
WATER
1,2-HEXANEDIOL
EUTERPE OLERACEA FRUIT EXTRACT
AUREOBASIDIUM PULLULANS FERMENT
WATER
BUTYLENE GLYCOL
HYDROGENATED LECITHIN
PANTHENOL
RAFFINOSE
1,2-HEXANEDIOL
FOLIC ACID
CERAMIDE NP
CHOLESTEROL
TROMETHAMINE
PALMITOYL PENTAPEPTIDE-4
WATER
BUTYLENE GLYCOL
GLYCERIN
CAPRYLYL GLYCOL
1,2-HEXANEDIOL
NONAPEPTIDE-1
PALMITOYL TETRAPEPTIDE-7
COPPER TRIPEPTIDE-1
ACETYL HEXAPEPTIDE-8
TRIPEPTIDE-1
HEXAPEPTIDE-9
PALMITOYL TRIPEPTIDE-1
PALMITOYL PENTAPEPTIDE-4
PROPANEDIOL
WATER
CAMELLIA JAPONICA FLOWER EXTRACT
ETHYLHEXYLGLYCERIN
TOCOPHEROL
ADENOSINE
DEXTRIN
THEOBROMA CACAO (COCOA) SEED EXTRACT
DISODIUM EDTA
MICROCRYSTALLINE CELLULOSE
CELLULOSE GUM
SODIUM HYALURONATE
WATER
GLYCERIN
1,2-HEXANEDIOL
BUTYLENE GLYCOL
PANAX GINSENG ROOT EXTRACT
ROSA CANINA FRUIT OIL
WATER
GLYCERIN
1,2-HEXANEDIOL
SOLUBLE COLLAGEN
METHYLPROPANEDIOL
FRAGARIA ANANASSA (STRAWBERRY) FRUIT JUICE
ALOE BARBADENSIS LEAF EXTRACT
PRUNUS SALICINA FRUIT EXTRACT
HYDROXYETHYL ACRYLATE/SODIUM ACRYLOYLDIMETHYL TAURATE COPOLYMER
SORBITAN ISOSTEARATE
POLYSORBATE 60
WATER
SCLEROCARYA BIRREA SEED OIL
CYANOCOBALAMIN

INDICATIONS AND USAGE

apply proper amount to the skin